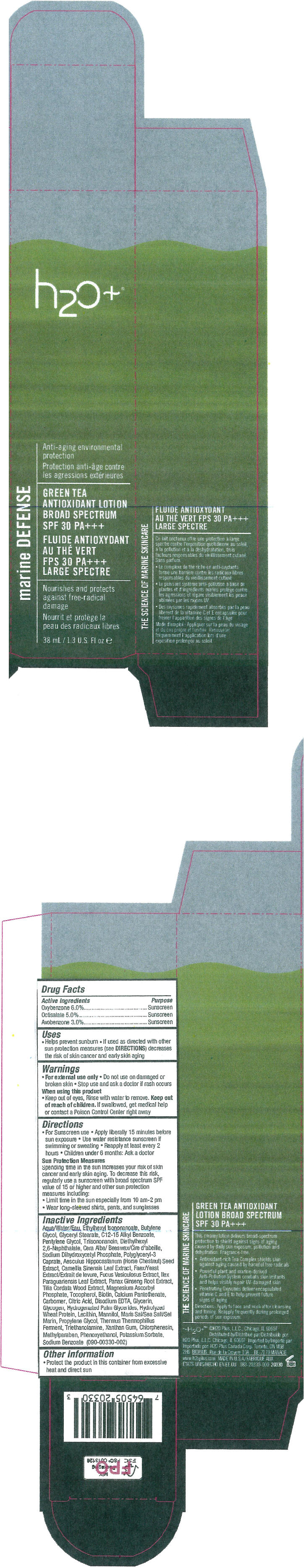 DRUG LABEL: Green Tea Antioxidant Broad Spectrum SPF 30 PAplusplusplus
NDC: 65903-330 | Form: LOTION
Manufacturer: H2O Plus LLC
Category: otc | Type: HUMAN OTC DRUG LABEL
Date: 20150226

ACTIVE INGREDIENTS: Oxybenzone 60 mg/1 mL; Octisalate 50 mg/1 mL; Avobenzone 30 mg/1 mL
INACTIVE INGREDIENTS: ETHYLHEXYL ISONONANOATE; Butylene Glycol; Glyceryl Monostearate; Alkyl (C12-15) Benzoate; Pentylene Glycol; Triisononanoin; DIETHYLHEXYL 2,6-NAPHTHALATE; Yellow Wax; Sodium Dihydroxycetyl Phosphate; Tilia Cordata Wood; Horse Chestnut; Green Tea Leaf; Yeast; Fucus Vesiculosus; Ilex Paraguariensis Leaf; Asian Ginseng; Magnesium Ascorbyl Phosphate; Tocopherol; Biotin; Calcium Pantothenate; CARBOMER HOMOPOLYMER TYPE C (ALLYL PENTAERYTHRITOL CROSSLINKED); Citric Acid Monohydrate; Edetate Disodium; Glycerin; Glycogen; Hydrogenated Palm Glycerides; LECITHIN, SOYBEAN; Mannitol; Sea Salt; Propylene Glycol; THERMUS THERMOPHILUS LYSATE; Trolamine; Xanthan Gum; Chlorphenesin; Methylparaben; Phenoxyethanol; Potassium Sorbate; Sodium Benzoate

Green Tea Antioxidant Broad Spectrum SPF 30 PA+++

Drug Facts

ACTIVE INGREDIENT

Active Ingredients | Purpose
Oxybenzone 6.0% | Sunscreen
Octisalate 5.0% | Sunscreen
Avobenzone 3.0% | Sunscreen

Uses

- Helps prevent sunburn
- If used as directed with other sun protection measures (see DIRECTIONS) decreases the risk of skin cancer and early skin aging

Warnings

- For external use only

- Do not use on damaged or broken skin

- Stop use and ask a doctor if rash occurs

When using this product

- Keep out of eyes, Rinse with water to remove.

Keep out of reach of children. If swallowed, get medical help or contact a Poison Control Center right away

Directions

- For Sunscreen use
- Apply liberally 15 minutes before sun exposure
- Use water resistance sunscreen if swimming or sweating
- Reapply at least every 2 hours
- Children under 6 months: Ask a doctor

Sun Protection Measures

Spending time in the sun increases your risk of skin cancer and early skin aging. To decrease this risk, regularly use a sunscreen with broad spectrum SPF value of 15 or higher and other sun protection measures including:

- Limit time in the sun especially from 10 am-2 pm
- Wear long-sleeved shirts, pants, and sunglasses

Inactive Ingredients

Aqua/Water/Eau, Ethylhexyl Isononanoate, Butylene Glycol, Glyceryl Stearate, C12-15 Alkyl Benzoate, Pentylene Glycol, Triisononanoin, Diethylhexyl 2,6-Naphthalate, Cera Alba/ Beeswax/Cire d'abeille, Sodium Dihydroxycetyl Phosphate, Polyglyceryl-3 Caprate, Aesculus Hippocastanum (Horse Chestnut) Seed Extract, Camellia Sinensis Leaf Extract, Faex/Yeast Extract/Extrait de levure, Fucus Vesiculosus Extract, Ilex Paraguariensis Leaf Extract, Panax Ginseng Root Extract, Tilia Cordata Wood Extract, Magnesium Ascorbyl Phosphate, Tocopherol, Biotin, Calcium Pantothenate, Carbomer, Citric Acid, Disodium EDTA, Glycerin, Glycogen, Hydrogenated Palm Glycerides, Hydrolyzed Wheat Protein, Lecithin, Mannitol, Maris Sal/Sea Salt/Sel Marin, Propylene Glycol, Thermus Thermophillus Ferment, Triethanolamine, Xanthan Gum, Chlorphenesin, Methylparaben, Phenoxyethanol, Potassium Sorbate, Sodium Benzoate (090-00330-002)

Other information

- Protect the product in this container from excessive heat and direct sun

Distributed by:
H2O Plus, L.L.C. Chicago, IL 60607

PRINCIPAL DISPLAY PANEL - 38 mL Bottle Carton

h2o+®

marine DEFENSE

Anti-aging environmental
protection

GREEN TEA
ANTIOXIDANT LOTION
BROAD SPECTRUM
SPF 30 PA+++

Nourishes and protects
against free-radical
damage

38 mL / 1.3 U.S. Fl oz e